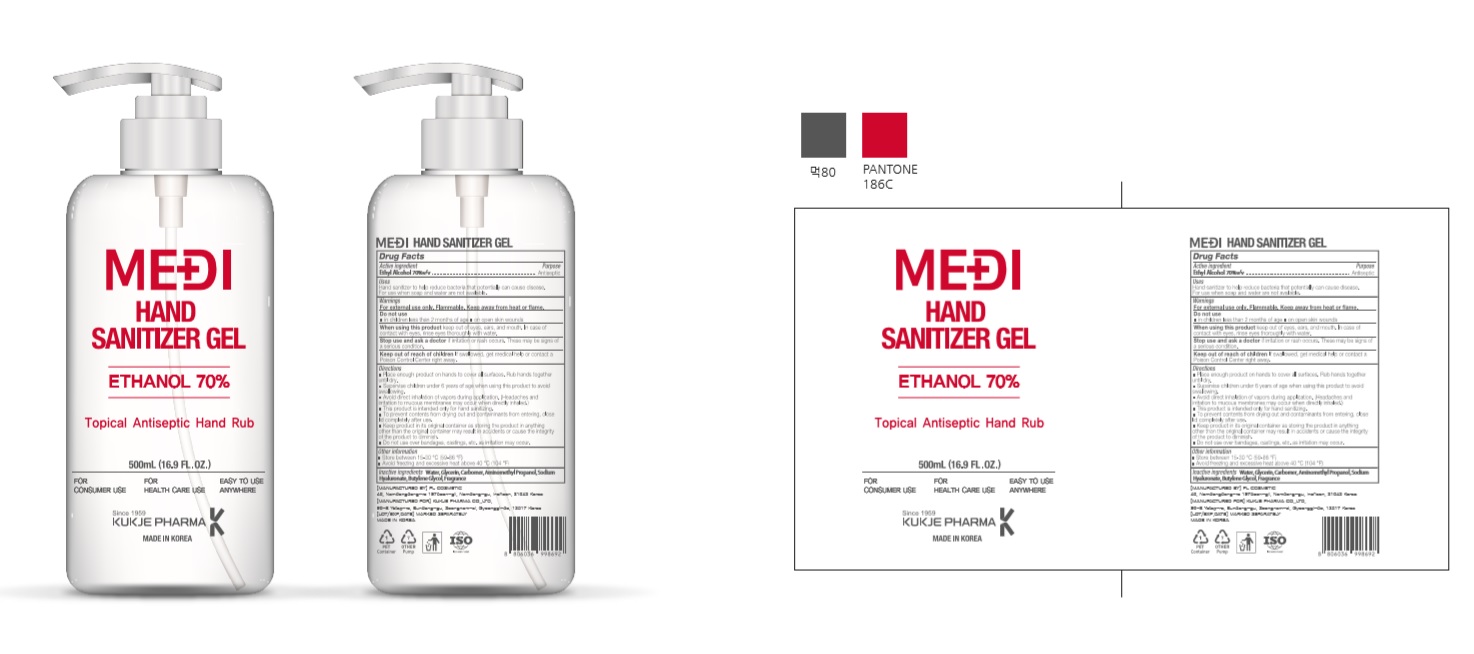 DRUG LABEL: MEDI HAND SANITIZER Gel
NDC: 74339-9500 | Form: GEL
Manufacturer: PL COSMETIC
Category: otc | Type: HUMAN OTC DRUG LABEL
Date: 20200422

ACTIVE INGREDIENTS: ALCOHOL 350 mL/500 mL
INACTIVE INGREDIENTS: GLYCERIN; CARBOMER HOMOPOLYMER, UNSPECIFIED TYPE; WATER; BUTYLENE GLYCOL; HYALURONATE SODIUM; AMINOMETHYLPROPANOL

[MEDI HAND SANITIZER Gel] 500 ml : 74339-9500-1